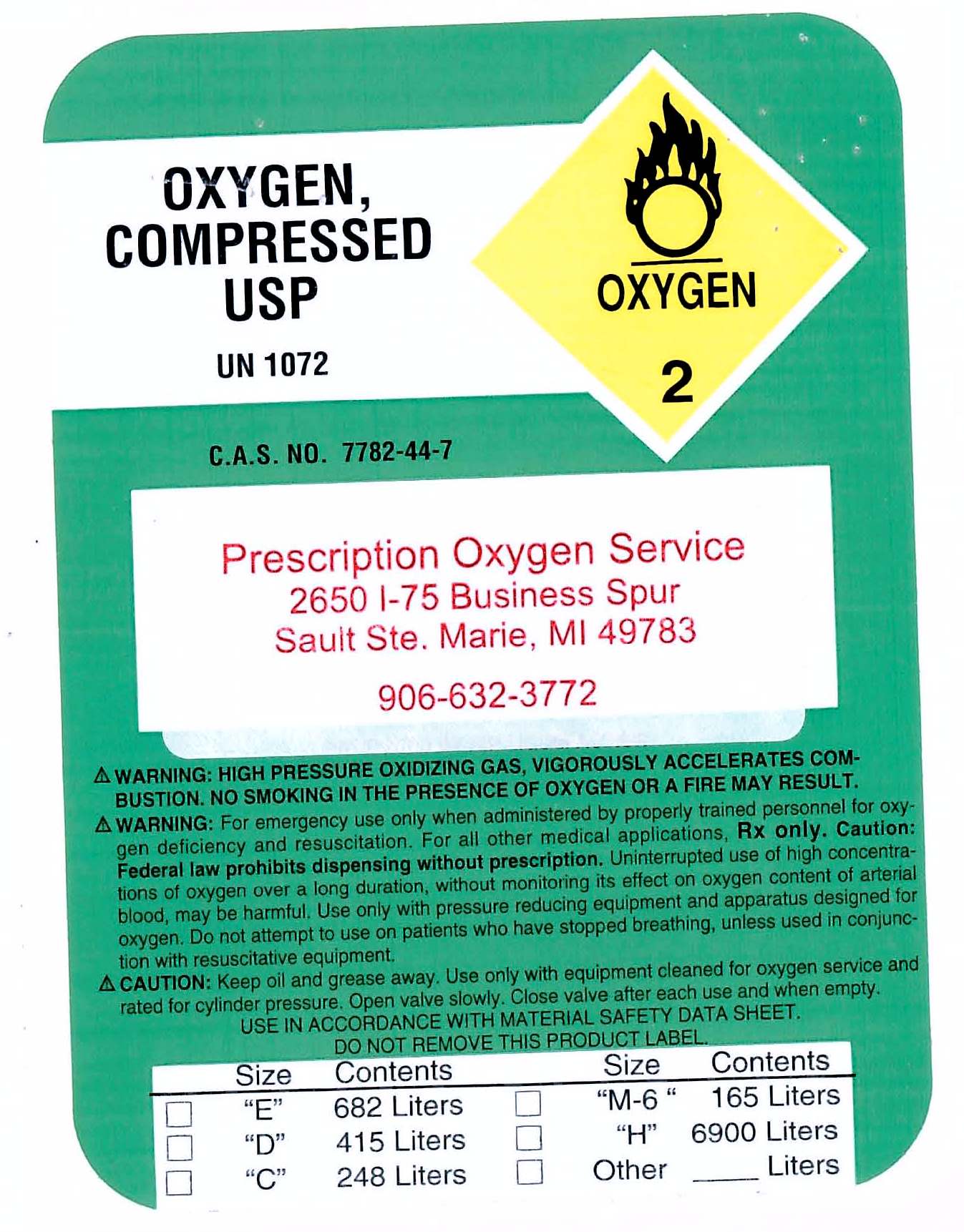 DRUG LABEL: Oxygen
NDC: 42654-001 | Form: GAS
Manufacturer: Prescription Oxygen Service
Category: prescription | Type: HUMAN PRESCRIPTION DRUG LABEL
Date: 20100621

ACTIVE INGREDIENTS: Oxygen 99 L/100 L

Oxygen